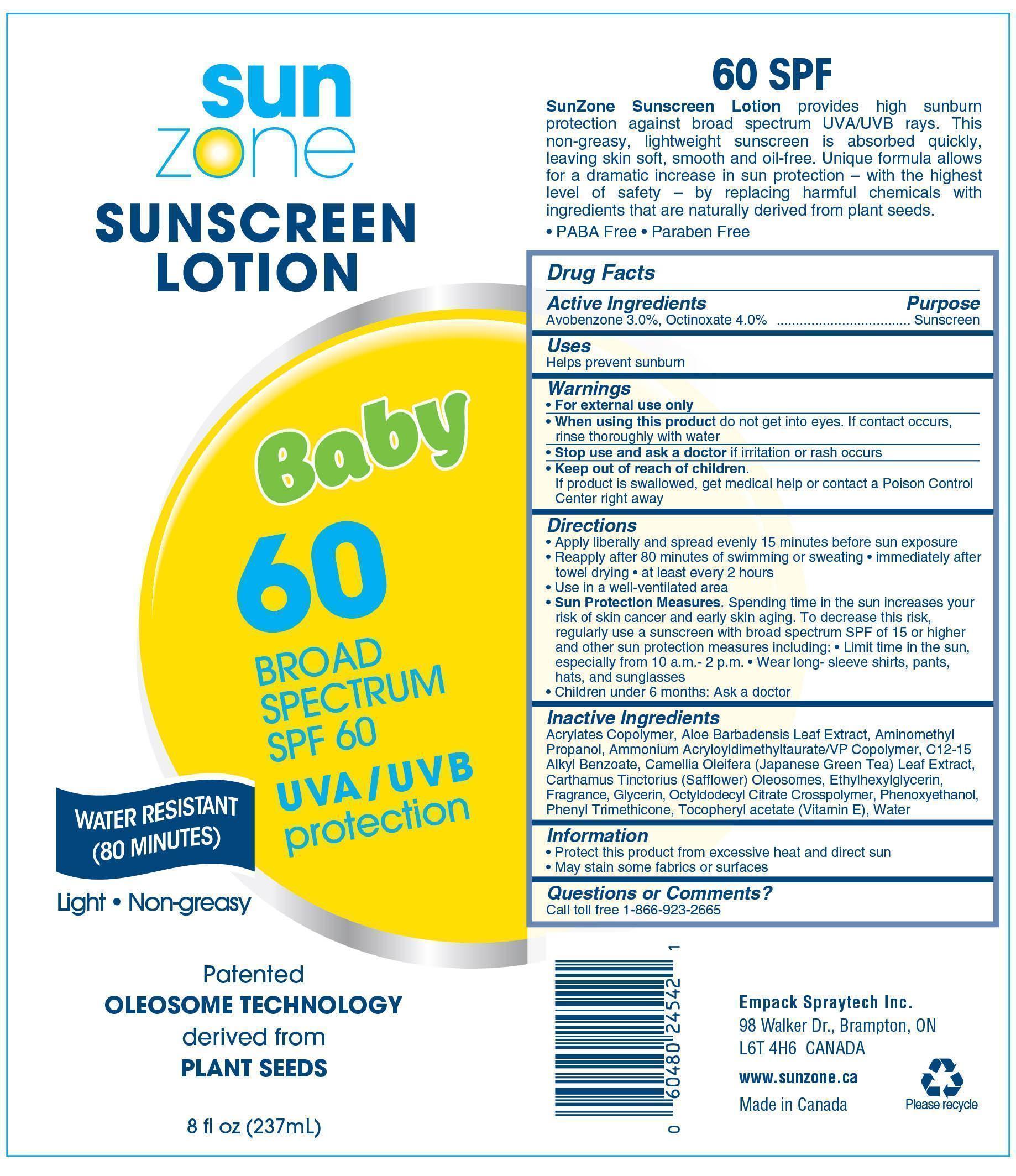 DRUG LABEL: SunZone Baby Sunscreen SPF-60
NDC: 50021-241 | Form: LOTION
Manufacturer: Empack Spraytech Inc.
Category: otc | Type: HUMAN OTC DRUG LABEL
Date: 20250210

ACTIVE INGREDIENTS: OCTINOXATE 9.36 g/234 g; AVOBENZONE 7.02 g/234 g
INACTIVE INGREDIENTS: CARTHAMUS TINCTORIUS (SAFFLOWER) OLEOSOMES; .ALPHA.-TOCOPHEROL ACETATE, DL-; PHENYL TRIMETHICONE; TRIOCTYLDODECYL CITRATE; WATER; ALOE VERA LEAF; CAMELLIA OLEIFERA LEAF; GLYCERIN; C12-15 ALKYL BENZOATE; PHENOXYETHANOL; ETHYLHEXYLGLYCERIN; AMMONIUM ACRYLOYLDIMETHYLTAURATE/VP COPOLYMER

50021-241 SunZone Baby Sunscreen SPF-60

Active Ingredients

Avobenzone......3%

Octinoxate........4%

Purpose

Sunscreen

Uses

Helps prevent sunburn

Warnings

For external use only

WHEN USING

When using the productdo not get into eyes. If contact occurs, rinse thoroughly with water

Stop use and ask a doctorif irritaion occurs

Keep out of reach of children

If product is swallowed, get medical help or contact a Posion Control Center right away

Directions

- Apply liberally and spread evenly 15 minutes before sun exposure
- Reapply after 80 minutes of swimmin or sweating
- immediately after swimming, towel drying
- At least every 2 hours

SUN PROTECTION MEASURES.Spending time in the sun increases your risk of skin cancer and early skin damage. To decrease this risk, regularly use a sunscreen with broad spectrum SPF 15 or higher and other sun protection measures including;

- Limit time in the sun, especially from 10 a.m-2p.m
- Wear long-sleeve shirts, pants, hats and sunglasses

Children under 6 months: ASK A DOCTOR

Inactive Ingredients

Acrylates Copolymer, Aloe Barbadensis Leaf Extract, Aminomethyl Propanol, Ammonium Acryloyldimethyltaurate/VP Copolymer, C12-15 Alkyl Benzoate, Camellia Oleifera (Japanese Green Tea) Leaf Extract, Carthamus Tinctorius (safflower) Oleosomes, dl-alpha Tocopheryl acetate, Ethylhexylglycerin, fragrance, glycerin, Octyldodecyl Citrate Crosspolymer, Phenoxyethanol, Phenyl Trimethicone, Water

Information

Protect this product from excessive heat and direct sun

May stain some fabrics or surfaces

Question or Comments

Call toll free 1-866-923-2665

Empack Spraytech Inc.

98 walker Drive, Brampton, Ontario

L6T 4H6

www.sunzone.ca

Made in Canada

Please Recycle

Directions

Apply liberally and spread evenly 15 minutes before sun exposure
Reapply after 80 minutes to swimming or sweating, Immediately after towel drying, at least every 2 hours
Use in a well ventilated areea
Sun Protection Measures: Spending time in the sun increases your risk of skin cancer and early skin aging. To decrease this risk, regularly use a sunscreen with broad spectrum SPF of 15 or higher and other sun protection measures including: Limit time in the sun, expectiron sfrom 10 a.m. to 2 p.m. Wear long sleeve shirts, pants, hats and sunglasses
Children under 6 months: Ask a doctor

Warning

For external use only